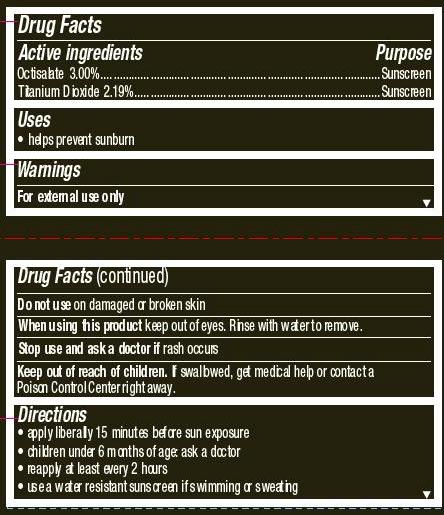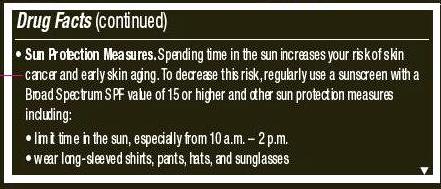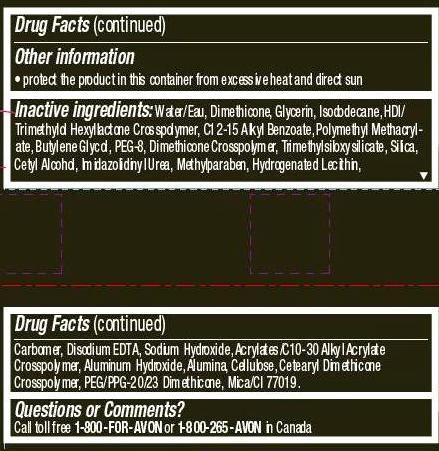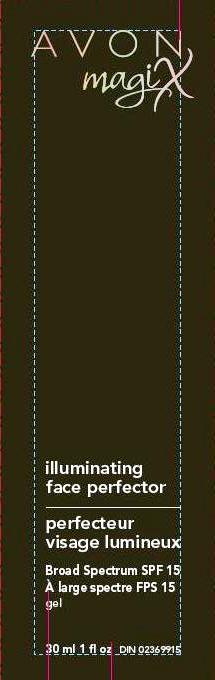 DRUG LABEL: magiX
NDC: 10096-0265 | Form: CREAM
Manufacturer: Avon Products, Inc.
Category: otc | Type: HUMAN OTC DRUG LABEL
Date: 20111220

ACTIVE INGREDIENTS: OCTISALATE	 0.9 mL/30 mL; TITANIUM DIOXIDE	 0.657 mL/30 mL

Drug Facts

Active ingredients
Octisalate 3.00%..................................................
Titanium Dioxide 2.19%..................................................

Purpose
....................................................Sunscreen
................................................Sunscreen

Uses
• helps prevent sunburn

Warnings
For external use only

Do not use on damaged or broken skin

When using this product keep out of eyes. Rinse with water to remove.

Stop use and ask a doctor if rash occurs

Keep out of reach of children. If swallowed, get medical help or contact a
Poison Control Center right away.

Directions
• apply liberally 15 minutes before sun exposure
• children under 6 months of age: ask a doctor
• reapply at least every 2 hours
• use a water resistant sunscreen if swimming or sweating

• Sun Protection Measures. Spending time in the sun increases your risk of skin
cancer and early skin aging. To decrease this risk, regularly use a sunscreen with a
Broad Spectrum SPF value of 15 or higher and other sun protection measures
including:
• limit time in the sun, especially from 10 a.m. – 2 p.m.
• wear long-sleeved shirts, pants, hats, and sunglasses

Other information
• protect the product in this container from excessive heat and direct sun

INACTIVE INGREDIENT

Inactive ingredients: Water/Eau, Dimethicone, Glycerin, Isododecane, HDI/Trimethylol Hexyllactone Crosspolymer, C12-15 Alkyl Benzoate, Polymethyl Methacrylate, Butylene Glycol, PEG-8, Dimethicone Crosspolymer, Trimethylsiloxysilicate, Silica, Cetyl Alcohol, Imidazolidinyl Urea, Methylparaben, Hydrogenated Lecithin,Carbomer, Disodium EDTA, Sodium Hydroxide, Acrylates/C10-30 Alkyl Acrylate Crosspolymer, Aluminum Hydroxide, Alumina, Cellulose, Cetearyl Dimethicone Crosspolymer, PEG/PPG-20/23 Dimethicone, Mica/CI 77019.

Questions or Comments?
Call toll free 1-800-FOR-AVON or 1-800-265-AVON in Canada